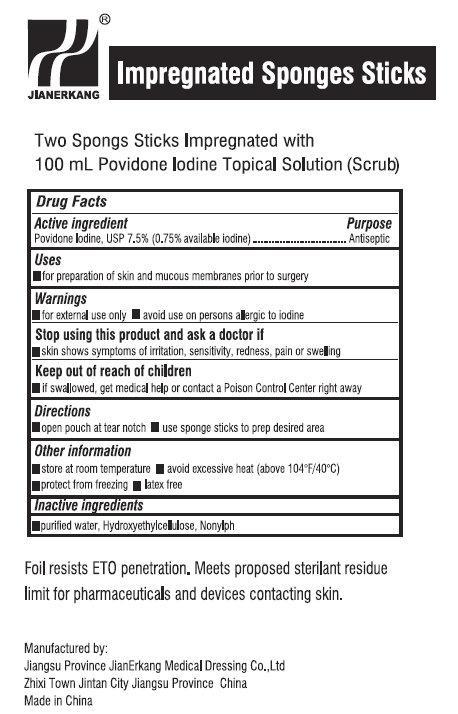 DRUG LABEL: Povidone Iodine Impregnated
NDC: 34645-1032 | Form: SPONGE
Manufacturer: Jianerkang Medical Co., Ltd
Category: otc | Type: HUMAN OTC DRUG LABEL
Date: 20231023

ACTIVE INGREDIENTS: POVIDONE-IODINE 7.5 mg/1 mL
INACTIVE INGREDIENTS: HYDROXYETHYL CELLULOSE (100 MPA.S AT 2%); WATER

Impregnated Winged Sponges - Two Sponges Sticks Impregnated with 100ml Providone Iodine (Scrub)

Active Ingredients

Povidone Iodine, USP 7.5% (0.75% available Iodine)

Purpose

Antiseptic

Uses

For preparation of skin and mucous membranes prior to surgery

Warnings

For external use only

Avoid use on persons allergic to iodine

Stop use and ask a doctor if

Skin shows symptoms of irritation, sensitivity, redness, pain or swelling

Keep out of reach of children

If swallowed, get medical help or contact Poison Control Center right away

Directions

open pouch at tear notch

use sponge sticks to prep desired area

Other information

store at room temperature avoid excessive heat (above 104 F/40 C) protect from freezing latex free
oo

Inactive Ingredients

purified water, hydroxyethylcellulose, Nonylph